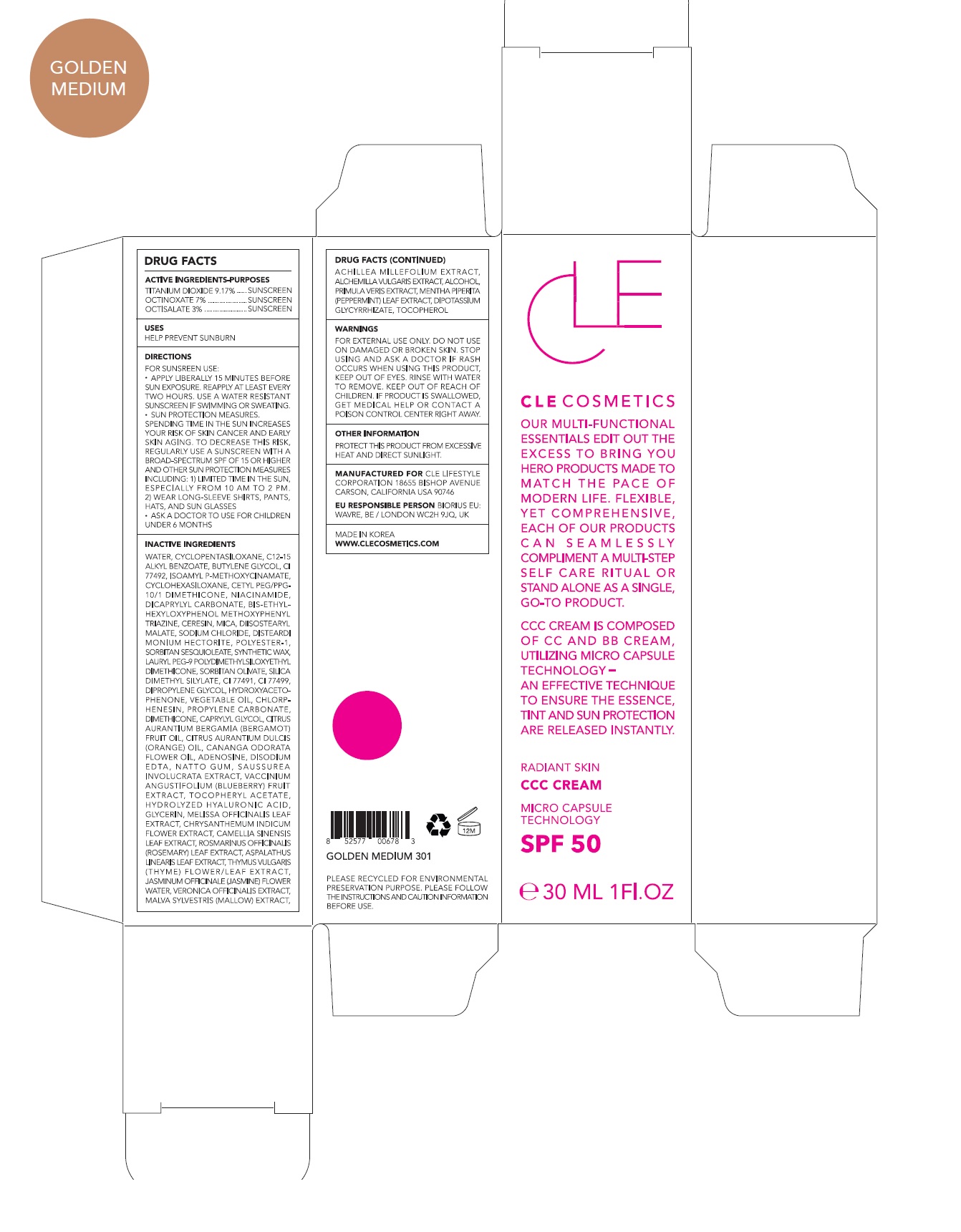 DRUG LABEL: CLE CCC Golden Medium
NDC: 69231-034 | Form: CREAM
Manufacturer: KW ABSC, INC.
Category: otc | Type: HUMAN OTC DRUG LABEL
Date: 20241219

ACTIVE INGREDIENTS: OCTINOXATE 2.1 mg/30 mL; OCTISALATE 0.9 mg/30 mL; TITANIUM DIOXIDE 2.751 mg/30 mL
INACTIVE INGREDIENTS: GLYCYRRHIZINATE DIPOTASSIUM; MALVA SYLVESTRIS FLOWERING TOP; WATER; CYCLOMETHICONE 5; ALKYL (C12-15) BENZOATE; BUTYLENE GLYCOL; AMILOXATE; CYCLOMETHICONE 6; CETYL PEG/PPG-10/1 DIMETHICONE (HLB 4); NIACINAMIDE; DICAPRYLYL CARBONATE; BEMOTRIZINOL; CERESIN; DIISOSTEARYL MALATE; SODIUM CHLORIDE; DISTEARDIMONIUM HECTORITE; SORBITAN SESQUIOLEATE; SYNTHETIC WAX (1200 MW); LAURYL PEG-9 POLYDIMETHYLSILOXYETHYL DIMETHICONE; SORBITAN OLIVATE; FERRIC OXIDE YELLOW; MICA; CHLORPHENESIN; DIPROPYLENE GLYCOL; HYDROXYACETOPHENONE; DIMETHICONE; CORN OIL; FERRIC OXIDE RED; CAPRYLYL GLYCOL; BERGAMOT OIL; ORANGE OIL; SILICA DIMETHYL SILYLATE; FERROSOFERRIC OXIDE; PHENYL TRIMETHICONE; ADENOSINE; YLANG-YLANG OIL; MELISSA OFFICINALIS LEAF; CHRYSANTHEMUM INDICUM FLOWER; GREEN TEA LEAF; EDETATE DISODIUM ANHYDROUS; ROSEMARY; ASPALATHUS LINEARIS LEAF; THYME; JASMINUM OFFICINALE FLOWER; LOWBUSH BLUEBERRY; .ALPHA.-TOCOPHEROL ACETATE; GLYCERIN; ACHILLEA MILLEFOLIUM WHOLE; ALCHEMILLA XANTHOCHLORA FLOWERING TOP; ALCOHOL; PRIMULA VERIS WHOLE; MENTHA PIPERITA LEAF; TOCOPHEROL

69231-034_CLE CCC Golden Medium

ACTIVE INGREDIENT

Titanium Dioxide 9.17%

Ethylhexyl Methoxycinnamate 7.00%

Ethylhexyl Salicylate 3.00%

PURPOSE

Sunscreen

INDICATIONS AND USAGE

Helps prevent sunburn

DOSAGE AND ADMINISTRATION

Apply liberally 15 minutes before sun exposure. Reapply at least every two hours

Sun protection measures. Spending time in the sun increases your risk of skin cancer and early skin aging. To decrease this risk, regularly use a sunscreen with a broad spectrum SPF of 15 of higher and other sun protection measures including: 1) Limited time in the sun, especially from 10 am to 2 pm. 2) Wear long-sleeve shirts, pants, hats, and sunglasses
Ask a doctor to use for children under 6 months

WARNINGS

For external use only.
Do not use on damaged or broken skin.
When using this product, keep out of eyes. Rinse with water to remove.
Stop using and ask a doctor if rash occurs.

KEEP OUT OF REACH OF CHILDREN

Keep out of reach of the children. If product is swallowed, get medical help or contact a poison control center right away.

INACTIVE INGREDIENT

Water, Cyclopentasiloxane, C12-15 Alkyl Benzoate, Butylene Glycol, CI 77492, Isoamyl p-Methoxycinnamate, Cyclohexasiloxane, Cetyl PEG/PPG-10/1 Dimethicone, Niacinamide, Dicaprylyl Carbonate, Bis-Ethylhexyloxyphenol Methoxyphenyl Triazine, Ceresin, Mica, Diisostearyl Malate, Sodium Chloride, Disteardimonium Hectorite, Polyester-1, Sorbitan Sesquioleate, Synthetic Wax, Lauryl PEG-9 Polydimethylsiloxyethyl Dimethicone, Sorbitan Olivate, Silica Dimethyl Silylate, CI 77491, CI 77499, Dipropylene Glycol, Hydroxyacetophenone, Vegetable Oil, Chlorphenesin, Propylene Carbonate, Dimethicone, Caprylyl Glycol, Citrus Aurantium Bergamia (Bergamot) Fruit Oil, Citrus Aurantium Dulcis (Orange) Oil, Cananga Odorata Flower Oil, Adenosine, Disodium EDTA, Natto Gum, Saussurea Involucrata Extract, Vaccinium Angustifolium (Blueberry) Fruit Extract, Tocopheryl Acetate, Hydrolyzed Hyaluronic Acid, Glycerin, Melissa Officinalis Leaf Extract, Chrysanthemum Indicum Flower Extract, Camellia Sinensis Leaf Extract, Rosmarinus Officinalis (Rosemary) Leaf Extract, Aspalathus Linearis Leaf Extract, Thymus Vulgaris (Thyme) Flower/Leaf Extract, Jasminum Officinale (Jasmine) Flower Water, Veronica Officinalis Extract, Malva Sylvestris (Mallow) Extract, Achillea Millefolium Extract, Alchemilla Vulgaris Extract, Alcohol, Primula Veris Extract, Mentha Piperita (Peppermint) Leaf Extract, Dipotassium, Glycyrrhizate, Tocopherol